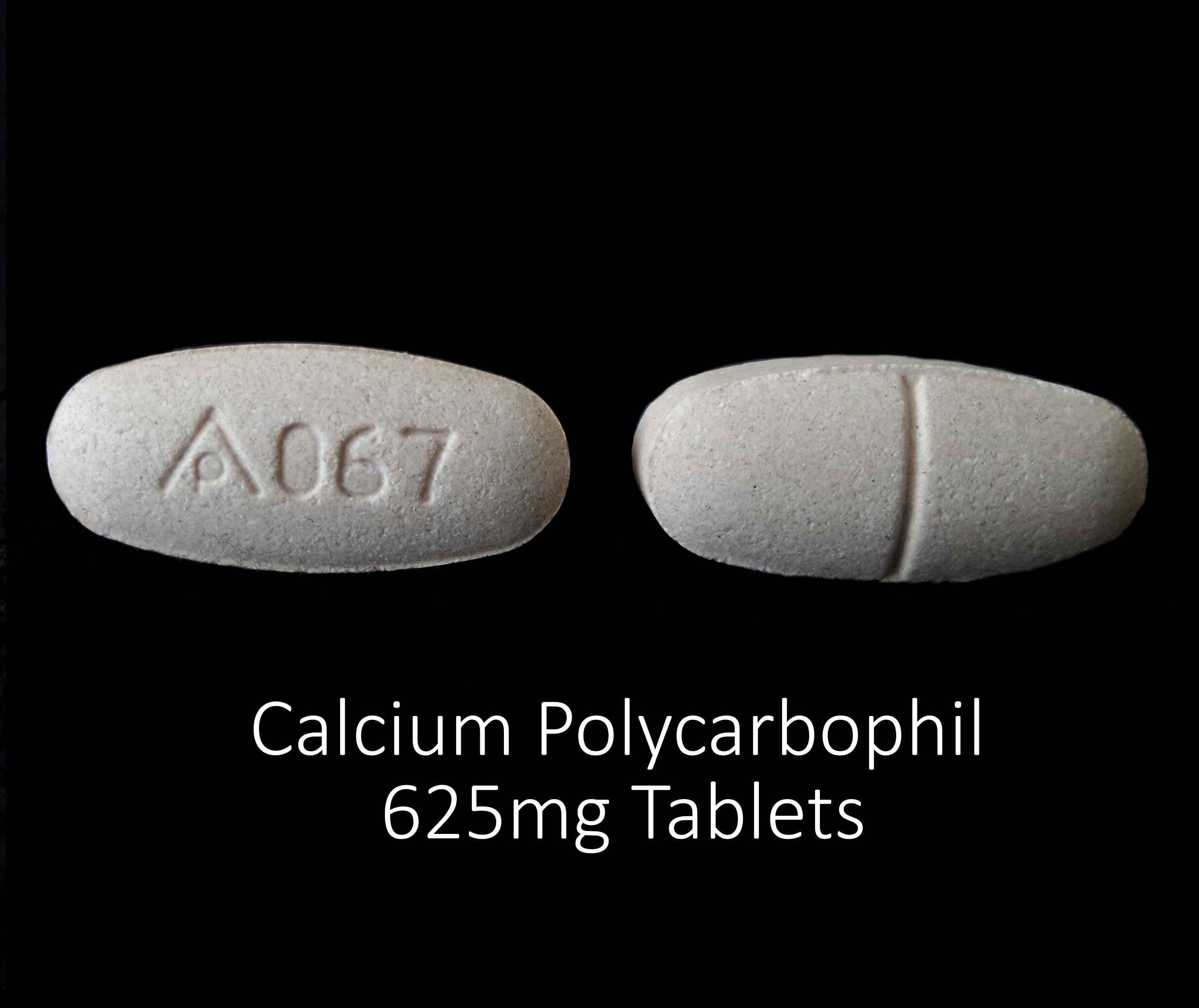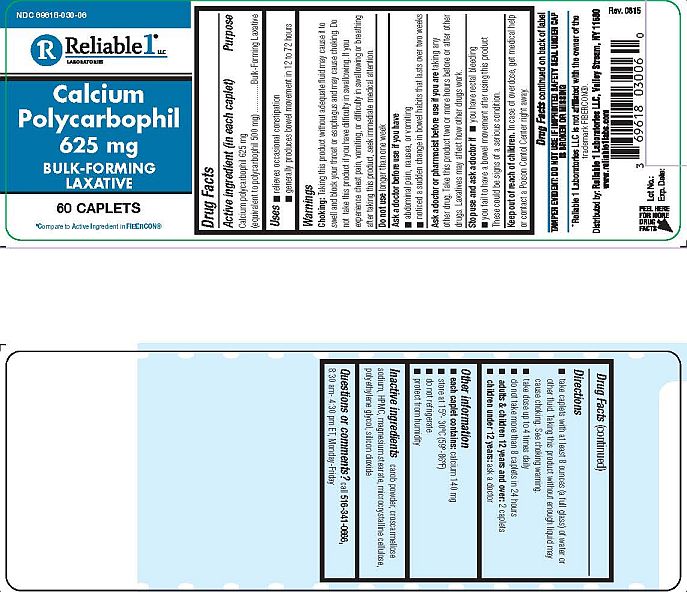 DRUG LABEL: Calcium Polycarbophil 625 mg
NDC: 69618-030 | Form: TABLET
Manufacturer: Reliable 1 Laboratories LLC
Category: otc | Type: HUMAN OTC DRUG LABEL
Date: 20211027

ACTIVE INGREDIENTS: CALCIUM POLYCARBOPHIL 625 mg/1 1
INACTIVE INGREDIENTS: CROSCARMELLOSE SODIUM; MAGNESIUM STEARATE; HYPROMELLOSES; CELLULOSE, MICROCRYSTALLINE; CAROB; SILICON DIOXIDE; POLYETHYLENE GLYCOL 1000

Calcium Polycarbophil 625 mg

Drug Facts

Active ingredient (in each caplet)

Calcium polycarbophil 625 mg

(equivalent to polycarbophil 500 mg)

Purpose

Bulk-Forming Laxative

Uses

- relieves occasional constipation
- generally produces bowel movement in 12 to 72 hours

Warnings

Choking: Taking this product without adequate fluid may cause it to swell and block your throat or esophagus and may cuase choking. Do not take this product if you have difficulty in swallowing. If you experience chest pain, vomiting, or difficulty in swallowing or breathing after taking this product, seek immediate medical attention.

Do not use longer than one week

Ask a doctor before use if you have

- abdominal pain, nausea, or vomiting
- noticed a sudden change in bowel habits that lasts over two weeks

Ask a doctor or pharmacist before use if you are taking any other drug. Take this product two or more hours before or after other drugs. Laxatives may affect how other drugs work.

Stop use and ask a doctor if

- you have rectal bleeding
- you fail to have a bowel movement after using this prodcut

These could be signs of a serious condition.

Keep out of reach of children. In case of overdose, get medical help or contact a Poison Control Center right away.

Drug Facts continued on back of label

Directions

- take caplets with at least 8 ounces (a full glass) of water or other fluid. Taking this prodcut without enough liquid may cause choking. See choking warning.
- take dose up to 4 times daily
- do not take more than 8 caplets in 24 hours
- adults & children 12 years and over: 2 caplets
- children under 12 years: ask a doctor

Other information

- each caplet contains: calcium 140 mg
- store at 15°-30°C (59°-86°F)
- do not refrigerate
- protect from humidity

INACTIVE INGREDIENT

Inactive ingredients carob powder, croscarmellose sodium, HPMC, magnesium stearate, microcrystalline cellulose, polyethylene glycol, silicon dioxide

Questions or comments? call 516-341-0666,

8:30 am - 4:30 pm ET, Monday-Friday

TAMPER EVIDENT: DO NOT USE IF IMPRINTED SAFETY SEAL UNDER CAP IS BROKEN OR MISSING

*Reliable 1 Laboratories LLC is not affiliated with the owner of the trademark FIBERCON®.

Distributed by: Reliable 1 Laboratories LLC, Valley Stream, NY 11580

www.reliablel1labs.com

PACKAGE LABEL

NDC 69618-030-06

Calcium Polycarbophil 625mg

Bulk-Forming Laxative

90 Caplets

*Compare to Active Ingredient in FIBERCON®